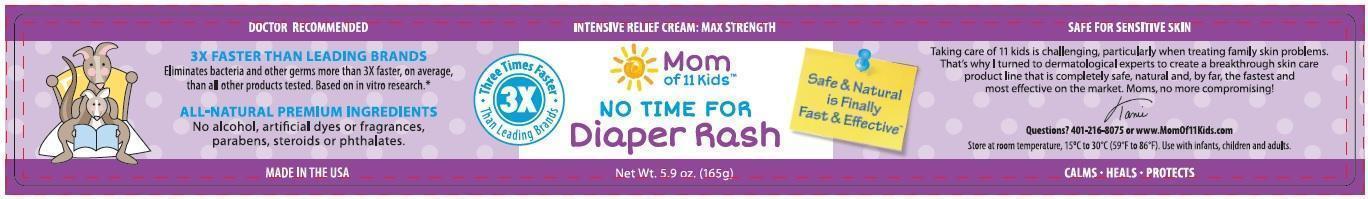 DRUG LABEL: Mom of 11 Kids No Time For Diaper Rash
NDC: 24909-502 | Form: OINTMENT
Manufacturer: Aidance Skincare & Topical Solutions, LLC
Category: homeopathic | Type: HUMAN OTC DRUG LABEL
Date: 20150820

ACTIVE INGREDIENTS: CALENDULA OFFICINALIS FLOWER 1 [hp_X]/100 g; COMFREY 1 [hp_X]/100 g; THUJA OCCIDENTALIS LEAF 6 [hp_X]/100 g
INACTIVE INGREDIENTS: ARGAN OIL; CHAMOMILE FLOWER OIL; COCONUT OIL; COTTONSEED OIL; JOJOBA OIL; GARCINIA INDICA FRUIT; MAGNESIUM OXIDE; OLIVE OIL; SILVER OXIDE; WHITE WAX; ZINC OXIDE

Drug Facts

Active Ingredients

Calendula 1X HPUS, Comfrey 1X HPUS, Thuja Occidentalis 6X HPUS

Purpose

Calendula - Healing agent
Comfrey - Inflammatory relief
Thuja Occidentalis - Skin protectant

Uses

Helps treat and prevent diaper rash. Protects chafed skin due to diaper rash.

Warnings

For external use only. Stop use and ask a doctor if condition worsens or if symptoms persist for more than 7 days, or clear up and occur again within a few days. When using this product avoid contact with eyes.

Keep out of reach of children.

If swallowed, get medical help or contact a Poison Control Center right away.

Directions

Change wet and soiled diapers promptly. Cleanse the diaper area, and allow to dry. Apply cream as liberally as necessary.

Inactive Ingredients

Argan Oil, Beeswax (organic), Chamomile Oil, Coconut Oil, Cotton Seed Oil, Jojoba Seed Oil (golden), Kokum Butter, Magnesium Oxide, Olive Oil, Silver Oxide, Zinc Oxide.

PRINCIPAL DISPLAY PANEL - 165g Label

Mom of 11 Kids™
NO TIME FOR™
Diaper Rash
Safe & Natural is Finally Fast & Effective™
Net Wt. 5.9 oz. (165g)